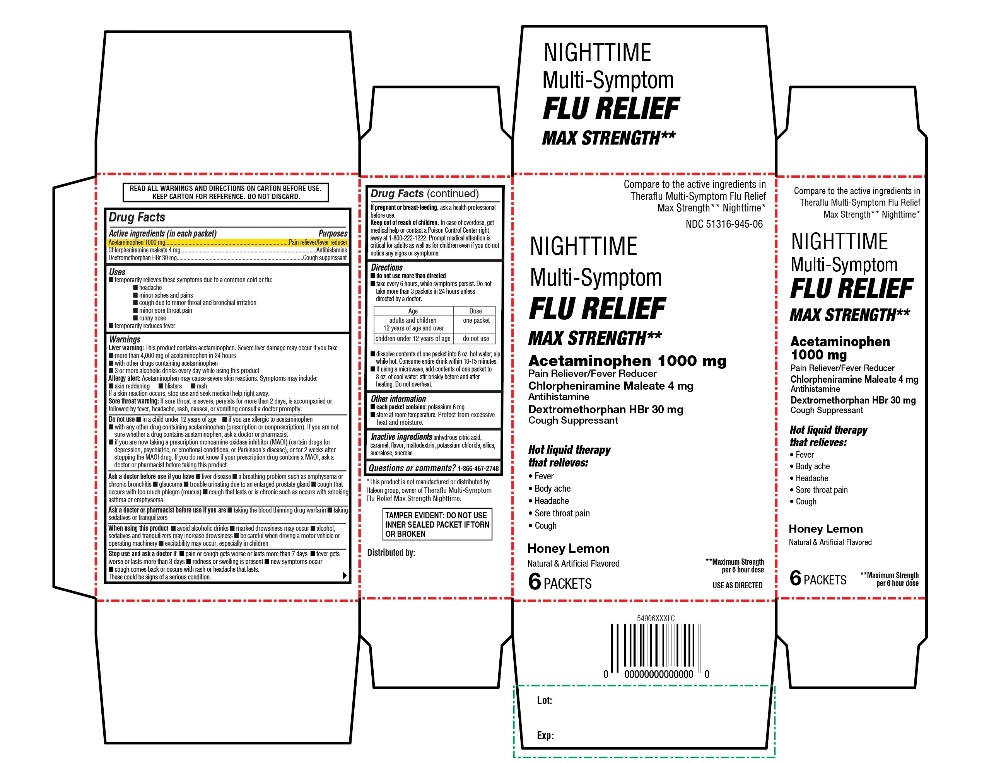 DRUG LABEL: CVS PHARMACY
NDC: 51316-945 | Form: POWDER, FOR SOLUTION
Manufacturer: CVS PHARMACY
Category: otc | Type: HUMAN OTC DRUG LABEL
Date: 20260227

ACTIVE INGREDIENTS: ACETAMINOPHEN 1000 mg/1 1; CHLORPHENIRAMINE MALEATE 4 mg/1 1; DEXTROMETHORPHAN HYDROBROMIDE 30 mg/1 1
INACTIVE INGREDIENTS: ANHYDROUS CITRIC ACID; CARAMEL; MALTODEXTRIN; POTASSIUM CHLORIDE; SILICON DIOXIDE; SUCRALOSE; SUCROSE

CVS Nighttime Multi-Symptom Flu Relief Max Strength Drug Facts

Active ingredients (in each packet)

Acetaminophen 1000 mg

Chlorpheniramine maleate 4 mg

Dextromethorphan HBr 30 mg

Purposes

Pain reliever/Fever reducer

Antihistamine

Cough suppressant

Uses

- temporarily relieves these symptoms due to a common cold or flu:
  - headache
  - minor aches and pains
  - cough due to minor throat and bronchial irritation
  - minor sore throat pain
  - runny nose
- temporarily reduces fever

Warnings

Liver warning: This product contains acetaminophen. Severe liver damage may occur if you take

- more than 4,000 mg of acetaminophen in 24 hours
- with other drugs containing acetaminophen
- 3 or more alcoholic drinks every day while using this product

Allergy alert: Acetaminophen may cause severe skin reactions. Symptoms may include:

- skin reddening
- blisters
- rash

If a skin reaction occurs, stop use and seek medical help right away.

Sore throat warning: If sore throat is severe, persists for more than 2 days, is accompanied or followed by fever, headache, rash, nausea, or vomiting consult a doctor promptly.

Do not use

- in a child under 12 years of age
- if you are allergic to acetaminophen
- with any other drug containing acetaminophen (prescription or nonprescription). If you are not sure whether a drug contains acetaminophen, ask a doctor or pharmacist.
- if you are now taking a prescription monoamine oxidase inhibitor (MAOI) (certain drugs for depression, psychiatric, or emotional conditions, or Parkinson’s disease), or for 2 weeks after stopping the MAOI drug. If you do not know if your prescription drug contains a MAO, ask a doctor or pharmacist before taking this product.

Ask a doctor before use if you have

- liver disease
- trouble urinating due to an enlarged prostate gland
- a breathing problem such as emphysema or chronic bronchitis
- cough that occurs with too much phlegm (mucus)
- cough that lasts or is chronic such as occurs with smoking, asthma, or emphysema

Ask a doctor or pharmacist before use if you are

- taking the blood thinning drug warfarin
- taking sedatives or tranquilizers

When using this product

- avoid alcoholic drinks
- marked drowsiness may occur
- alcohol, sedatives, and tranquilizers may increase drowsiness
- be careful when driving a motor vehicle or operating machinery
- excitability may occur, especially in children

Stop use and ask a doctor if

- pain or cough gets worse or lasts more than 7 days
- fever gets worse or lasts more than 3 days
- redness or swelling is present
- new symptoms occur
- cough comes back or occurs with rash or headache that lasts.
These could be signs of a serious condition.

If pregnant or breast-feeding,

ask a health professional before use.

Keep out of reach of children.

In case of overdose, get medical help or contact a Poison Control Center right away at 1-800-222-1222. Prompt medical attention is critical for adults as well as for children even if you do not notice any signs or symptoms.

Directions

- do not use more than directed
- take every 6 hours, while symptoms persist. Do not take more than 3 packets in 24 hours unless directed by a doctor.

Age | Dose
adults and children 12 years of age and over | one packet
children under 12 years of age | do not use

- dissolve contents of one packet into 8 oz. hot water; sip while hot. Consume entire drink within 10-15 minutes.
- if using a microwave, add contents of one packet to 8 oz. of cool water; stir briskly before and after heating. Do not overheat

Other information

- each packet contains: potassium 6 mg
- store at room temperature. Protect from excessive heat and moisture.

Inactive ingredients

anhydrous citric acid, Caramel, flavor, maltodextrin, potassium chloride, silica, sucralose, sucrose

Questions or comments?

1-866-467-2748

Principal Display Panel

Compare to the active ingredients in Theraflu Multi-Symptom Flu Relief Max Strength** Nighttime*

NDC 51316-945-06

Nighttime

Multi-Symptom

Flu Relief

MAX STRENGTH**

Acetaminophen 1000 mg - Pain Reliever/Fever Reducer

Chlorpheniramine Maleate 4 mg - Antihistamine

Dextromethorphan HBr 30 mg - Cough Suppressant

Hot Liquid therapy that relieves:

- Fever
- Body ache
- Headache
- Sore throat pain
- Cough

Honey Lemon

Natural & Artificial Flavored

6 PACKAETS

**Maximum Strength per 6 hours dose

READ ALL WARNINGS AND DIRECTIONS ON CARTON BEFORE USE. KEEP CARTON FOR REFERENCE. DO NOT DISCARD.

TAMPER EVIDENT: DO NOT USE INNER SEALED PACKET IF TORN OR BROKEN.

*This product is not manufactured or distributed by Haleon group, owner of Theraflu Multi-Symptom Flu Relief Max Strength** Nighttime.

Manufactured by: